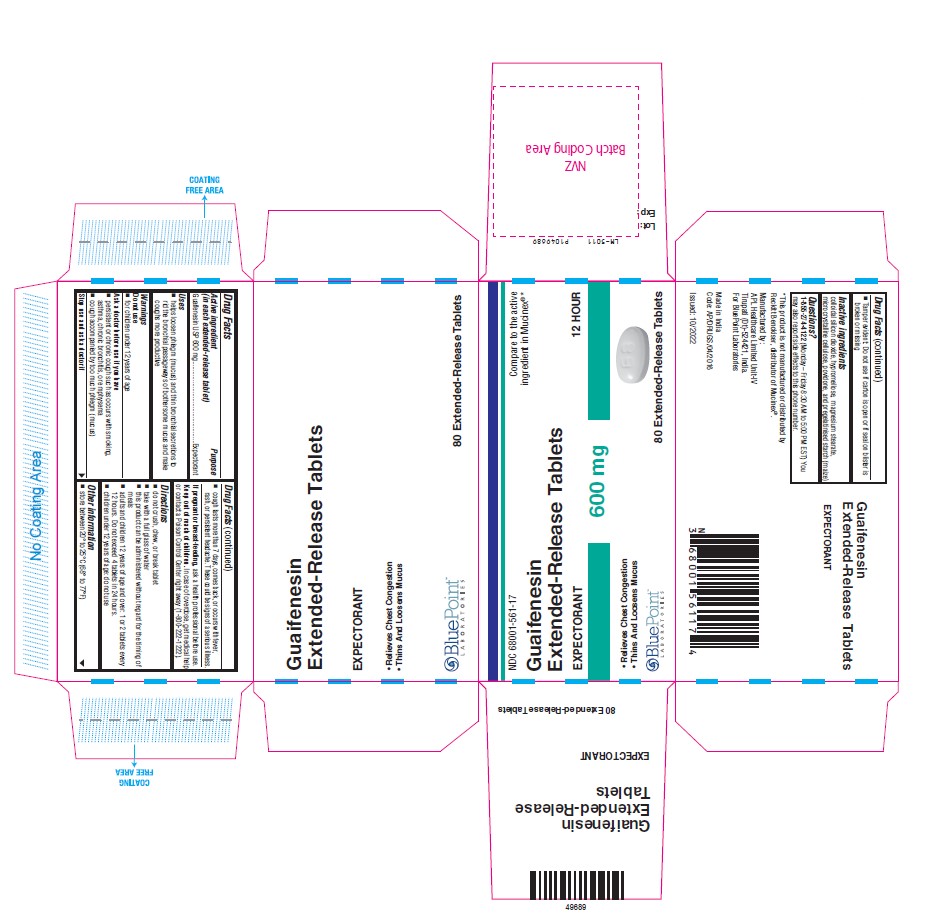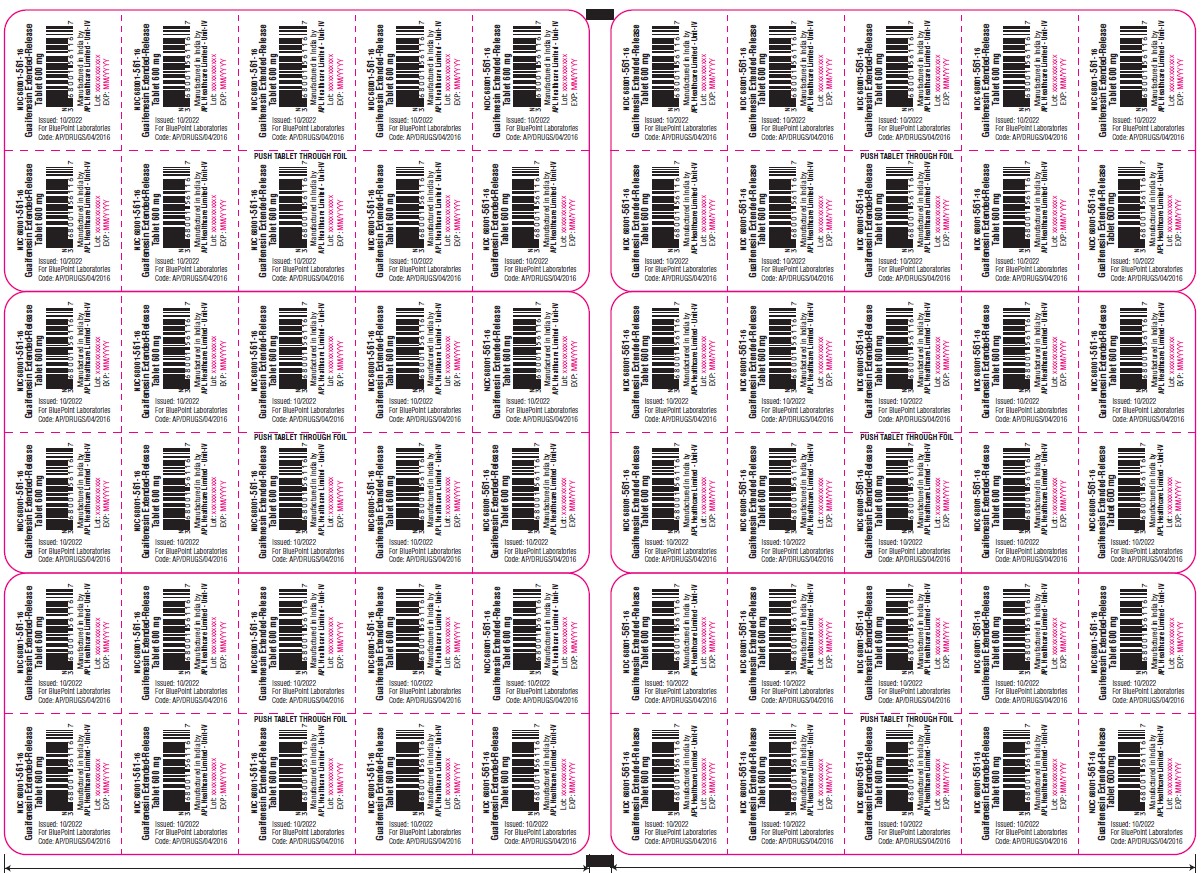 DRUG LABEL: Guaifenesin
NDC: 68001-561 | Form: TABLET, EXTENDED RELEASE
Manufacturer: BluePoint Laboratories
Category: otc | Type: HUMAN OTC DRUG LABEL
Date: 20231212

ACTIVE INGREDIENTS: GUAIFENESIN 600 mg/1 1
INACTIVE INGREDIENTS: SILICON DIOXIDE; HYPROMELLOSE 2208 (15000 MPA.S); HYPROMELLOSE 2910 (10000 MPA.S); MAGNESIUM STEARATE; MICROCRYSTALLINE CELLULOSE 101; MICROCRYSTALLINE CELLULOSE 102; POVIDONE K90; POVIDONE K25; STARCH, CORN

Guaifenesin Extended Release Tablets 600 mg

Active ingredient

(in each extended-release tablet)
Guaifenesin USP 600 mg

Purpose

Expectorant

Uses

- helps loosen phlegm (mucus) and thin bronchial secretions to rid the bronchial passageways of bothersome mucus and make coughs more productive

Warnings

Do not use

- for children under 12 years of age

Ask a doctor before use if you have

- persistent or chronic cough such as occurs with smoking, asthma, chronic bronchitis, or emphysema
- cough accompanied by too much phlegm (mucus)

Stop use and ask a doctor if

- cough lasts more than 7 days, comes back, or occurs with fever, rash, or persistent headache. These could be signs of a serious illness.

If pregnant or breast-feeding,

ask a health professional before use.

Keep out of reach of children

In case of overdose, get medical help or contact a Poison Control Center right away (1-800-222-1222).

Directions

- do not crush, chew, or break tablet
- take with a full glass of water
- this product can be administered without regard for the timing of meals
- adults and children 12 years of age and over: 1 or 2 tablets every 12 hours. Do not exceed 4 tablets in 24 hours.
- children under 12 years of age: do not use

Other information

- store between 20° to 25°C (68° to 77°F)

Inactive ingredients

colloidal silicon dioxide, hypromellose, magnesium stearate, microcrystalline cellulose, povidone, and pregelatinised starch (maize)

Questions?

1-855-274-4122(Monday – Friday 8:30 AM to 5:00 PM EST) You may also report side effects to this phone number.

Manufactured by:
APL Healthcare Limited Unit-IV.
Tirupati (Dt) - 524421, India
For BluePoint Laboratories
Made in India

Code: AP/DRUGS/04/2016

Rev: 10/2022

PACKAGE LABEL-PRINCIPAL DISPLAY PANEL - 600 mg Blister Foil and 600 mg Carton (80 Extended-Release Tablets, 1x10's).

Blister Pack : NDC 68001-561-16

Carton Pack : NDC 68001-561-17
Guaifenesin Extended-Release Tablets 600 mg
EXPECTORANT
12 HOUR

- Relieves Chest Congestion
- Thins And Loosens Mucus

80 Extended-Release Tablets